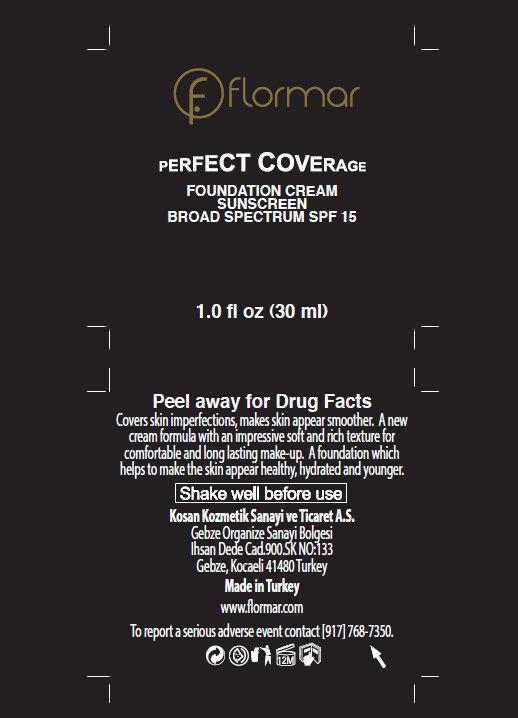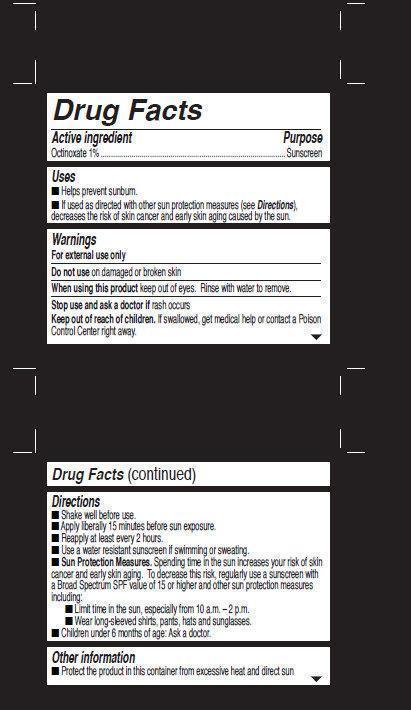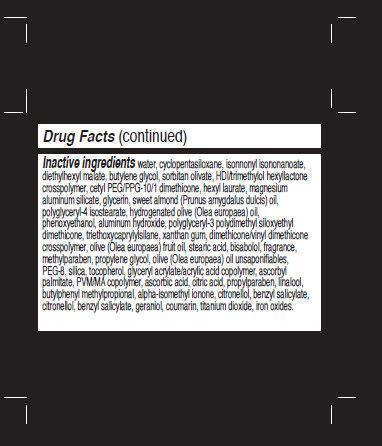 DRUG LABEL: flormar PERFECT COVERAGE FOUNDATION SUNSCREEN BROAD SPECTRUM SPF 15 102 Soft Beige
NDC: 61722-081 | Form: CREAM
Manufacturer: Kosan Kozmetik Sanayi ve Ticaret A.S.
Category: otc | Type: HUMAN OTC DRUG LABEL
Date: 20191018

ACTIVE INGREDIENTS: OCTINOXATE 10 mg/1 mL
INACTIVE INGREDIENTS: WATER; CYCLOMETHICONE 5; ISONONYL ISONONANOATE; DIETHYLHEXYL MALEATE; BUTYLENE GLYCOL; SORBITAN OLIVATE; HEXYL LAURATE; MAGNESIUM ALUMINUM SILICATE; GLYCERIN; ALMOND OIL; POLYGLYCERYL-4 ISOSTEARATE; OLIVE OIL; PHENOXYETHANOL; ALUMINUM HYDROXIDE; TRIETHOXYCAPRYLYLSILANE; XANTHAN GUM; STEARIC ACID; LEVOMENOL; METHYLPARABEN; PROPYLENE GLYCOL; POLYETHYLENE GLYCOL 400; SILICON DIOXIDE; TOCOPHEROL; ASCORBYL PALMITATE; ASCORBIC ACID; CITRIC ACID MONOHYDRATE; PROPYLPARABEN; LINALOOL, (+/-)-; BUTYLPHENYL METHYLPROPIONAL; ISOMETHYL-.ALPHA.-IONONE; .BETA.-CITRONELLOL, (R)-; BENZYL SALICYLATE; GERANIOL; COUMARIN; TITANIUM DIOXIDE

flormar PERFECT COVERAGE FOUNDATION CREAM SUNSCREEN BROAD SPECTRUM SPF 15 102 Soft Beige

Active ingredient

Octinoxate 1%

Purpose

Sunscreen

Uses

- Helps prevent sunburn.
- If used as directed with other sun protection measures (see Directions), decreases the risk of skin cancer and early skin aging caused by the sun.

Warnings

For external use only

Do not use

on damaged or brokenskin

When using this product

keep out of eyes. Rinse with water to remove.

Stop use and ask a doctor if

rash occurs

Keep out of reach of children.

If swallowed, get medical help or contact a Poison Control Center right away.

Directions

- Shake well before use.
- Apply liberally 15 minutes before sun exposure.
- Reapply at least every 2 hours.
- Use a water resistant sunscreen if swimming or sweating.
- Sun Protection Measures. Spending time in the sun increases your risk of skin cancer and early skin aging. To decrease this risk, regularly use a sunscreen with a Broad Spectrum SPF value of 15 or higher and other sun protection measures including:
-
  - Limit time in the sun, especially from 10 a.m. – 2 p.m.
  - Wear long-sleeved shirts, pants, hats and sunglasses.
- Children under 6 months of age: Ask a doctor.

Other information

- Protect the product in this container from excessive heat and direct sun

Inactive ingredients

- water, cyclopentasiloxane, isonnonyl isononanoate, diethylhexyl malate, butylene glycol, sorbitan olivate, HDI/trimethylol hexyllactone crosspolymer, cetyl PEG/PPG-10/1 dimethicone, hexyl laurate, magnesium aluminum silicate, glycerin, sweet almond (Prunus amygdalus dulcis) oil, polyglyceryl-4 isostearate, hydrogenated olive (Olea europaea) oil, phenoxyethanol, aluminum hydroxide, polyglyceryl-3 polydimethyl siloxyethyl dimethicone, triethoxycaprylylsilane, xanthan gum, dimethicone/vinyl dimethicone crosspolymer, olive (Olea europaea) fruit oil, stearic acid, bisabolol, fragrance, methylparaben, propylene glycol, olive (Olea europaea) oil unsaponifiables, PEG-8, silica, tocopherol, glyceryl acrylate/acrylic acid copolymer, ascorbyl palmitate, PVM/MA copolymer, ascorbic acid, citric acid, propylparaben, linalool, butylphenyl methylpropional, alpha-isomethyl ionone, citronellol, benzyl salicylate, citronellol, benzyl salicylate, geraniol, coumarin, titanium dioxide, iron oxides.